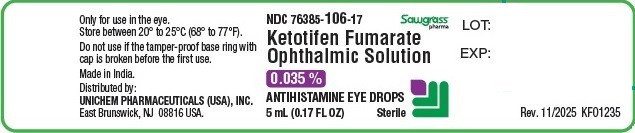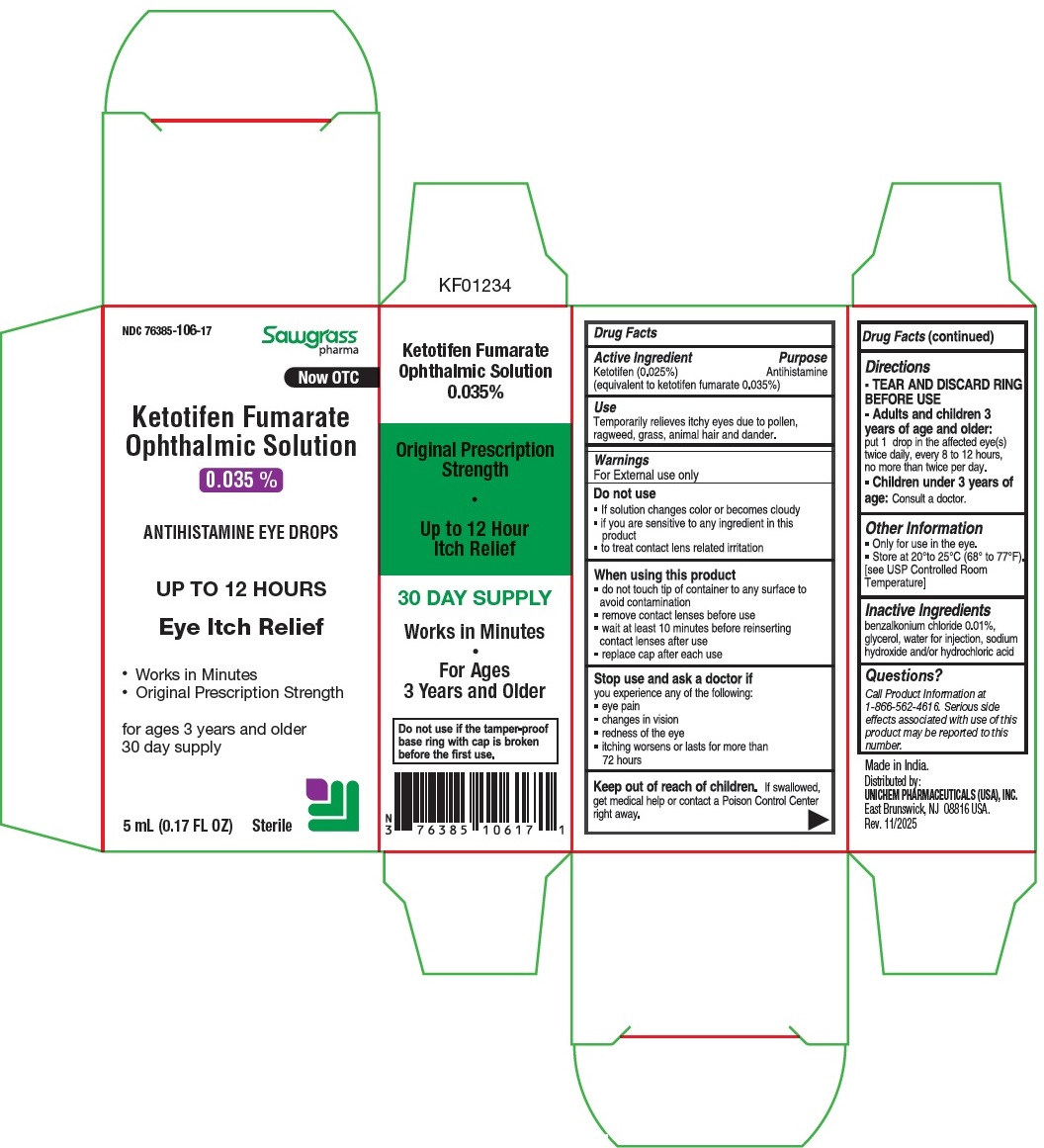 DRUG LABEL: KETOTIFEN FUMARATE
NDC: 76385-106 | Form: SOLUTION
Manufacturer: Unichem Pharmaceuticals (USA), Inc.
Category: otc | Type: HUMAN OTC DRUG LABEL
Date: 20251124

ACTIVE INGREDIENTS: KETOTIFEN FUMARATE 0.25 mg/1 mL
INACTIVE INGREDIENTS: GLYCERIN; SODIUM HYDROXIDE; HYDROCHLORIC ACID; BENZALKONIUM CHLORIDE

Drug Facts

Active ingredient

Ketotifen (0.025%)

(equivalent to ketotifen fumarate 0.035%)

Purpose

Antihistamine

Use

Temporarily relieves itchy eyes due to pollen, ragweed, grass, animal hair and dander.

Warnings

For external use only

Do not use

- if solution changes color or becomes cloudy
- if you are sensitive to any ingredient in this product
- to treat contact lens related irritation

When using this product

- do not touch tip of container to any surface to avoid contamination
- remove contact lenses before use
- wait at least 10 minutes before reinserting contact lenses after use
- replace cap after each use

Stop use and ask a doctor if you experience any of the following:

- eye pain
- changes in vision
- redness of the eye
- itching worsens or lasts for more than 72 hours

Keep out of reach of children.

If swallowed, get medical help or contact a Poison Control Center right away.

Directions

- Adults and children 3 years of age and older: Put 1 drop in the affected eye(s) twice daily, every 8 to 12 hours, no more than twice per day.
- Children under 3 years of age: Consult a doctor.

Other information

- Only for use in the eye.
- Store at 20°C to 25°C (68°F to 77°F) [see USP Controlled Room Temperature].

Inactive ingredients

benzalkonium chloride 0.01%, glycerol, water for injection, sodium hydroxide and/or hydrochloric acid.

Questions?

Call Product Information at 1-866-562-4616. Serious side effects associated with use of this product may be reported to this number.

Made in India

Distributed by:

UNICHEM PHARMACEUTICALS (USA), INC.

East Brunswick, NJ 08816 USA

Rev. 11/2025

KFO1236

PACKAGE LABEL.PRINCIPAL DISPLAY PANEL

NDC 76385-106-17

Ketotifen Fumarate Opthalmic Solution 0.035%

ANTIHISTAMINE EYE DROPS

5 mL (0.17 FL OZ)

Sterile

PACKAGE LABEL.PRINCIPAL DISPLAY PANEL

NDC 76385-106-17

Now OTC

Ketotifen Fumarate Opthalmic Solution 0.035%

ANTIHISTAMINE EYE DROPS

UP TO 12 HOURS

Eye Itch Relief

Works in Minutes

Original Prescription Strength

for ages 3 years and older

20 day supply

5 mL (0.17 FL OZ)

Sterile